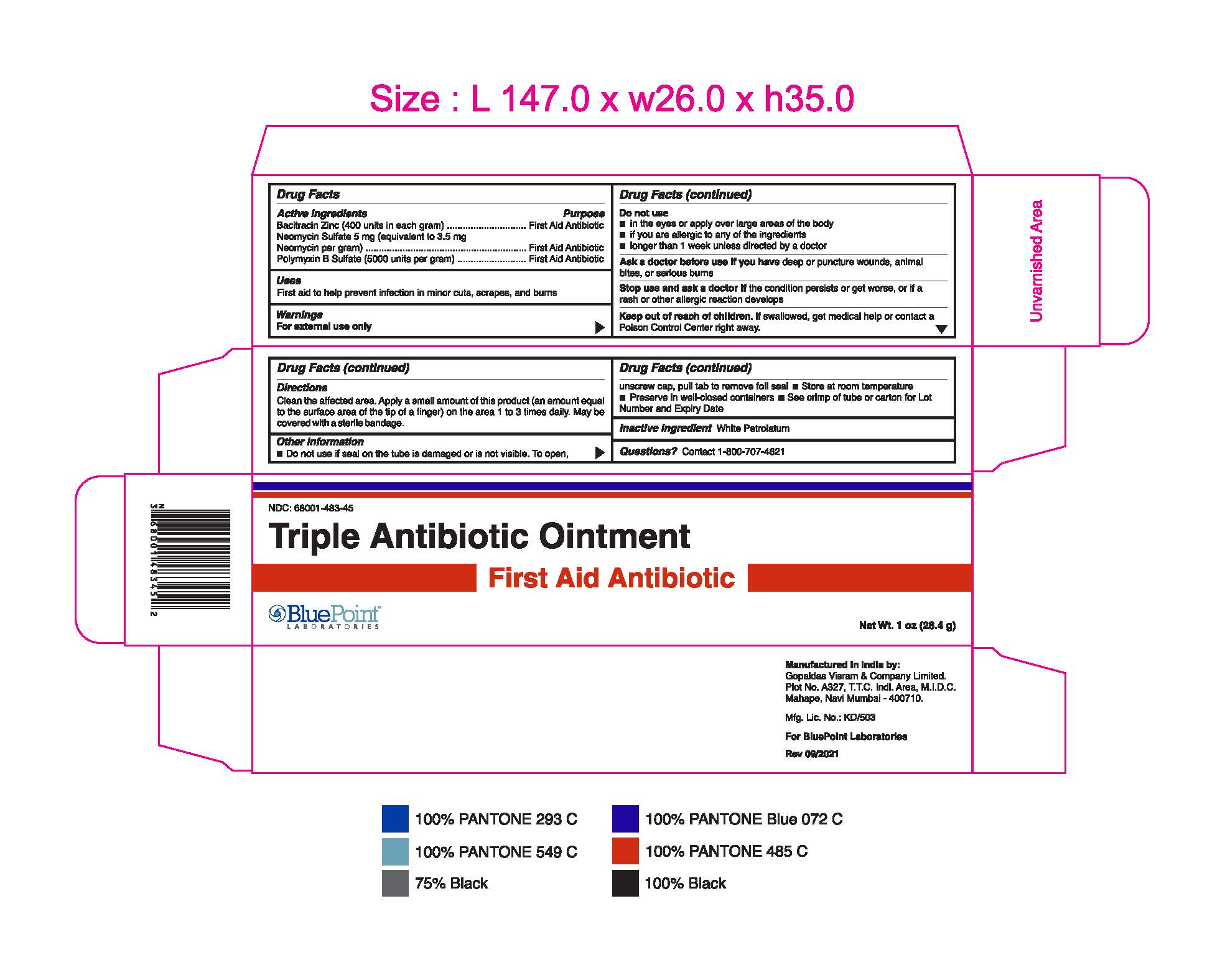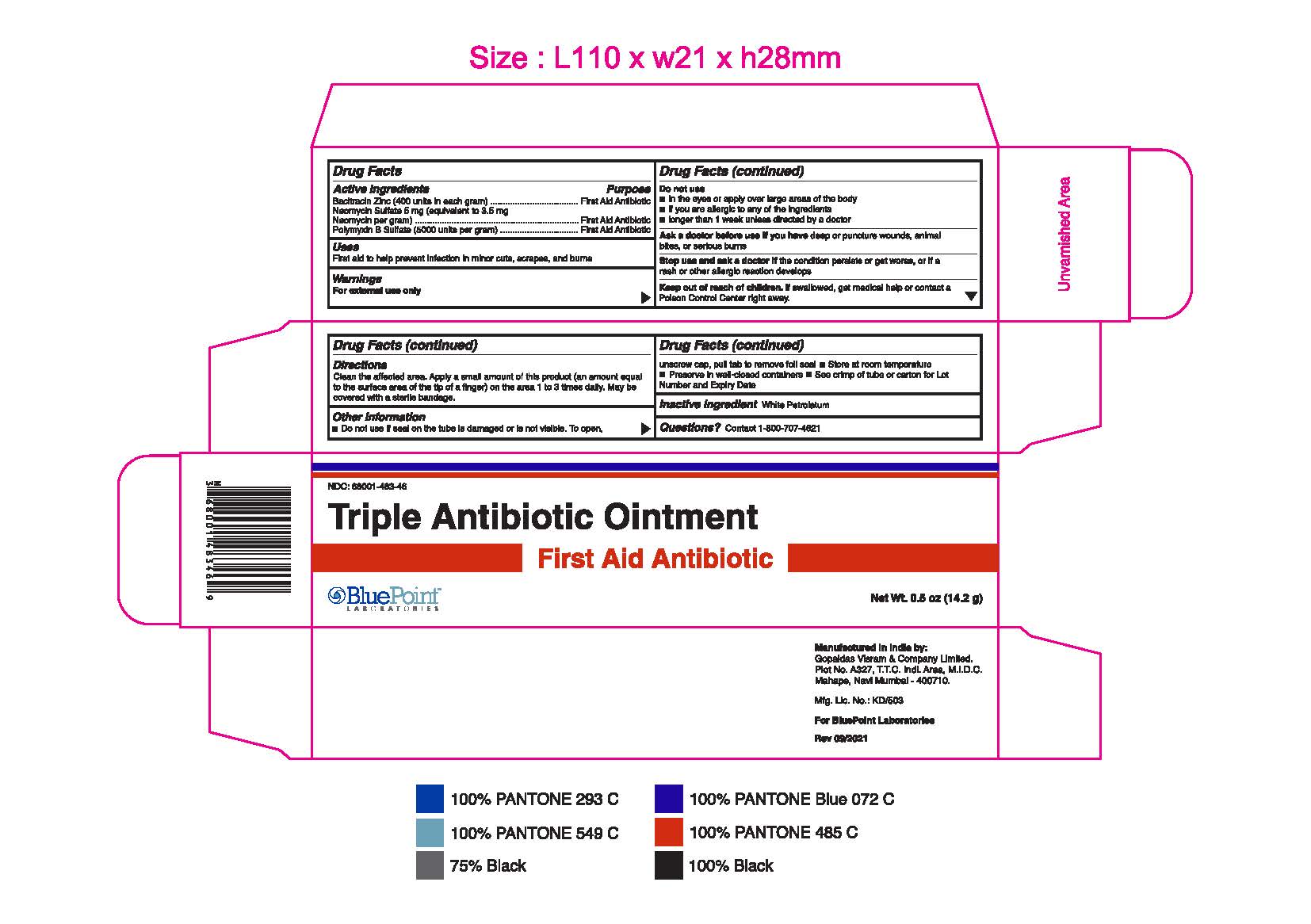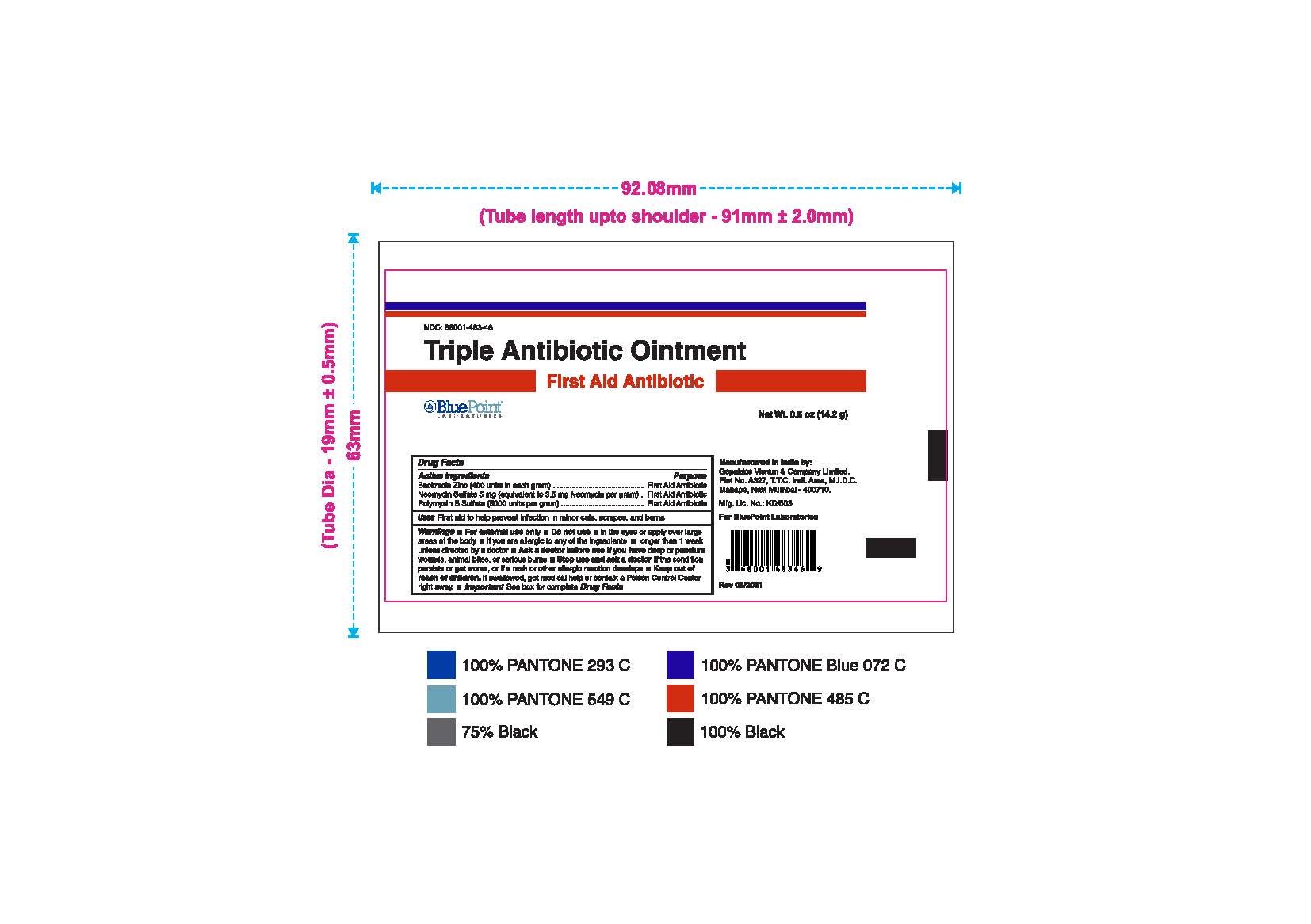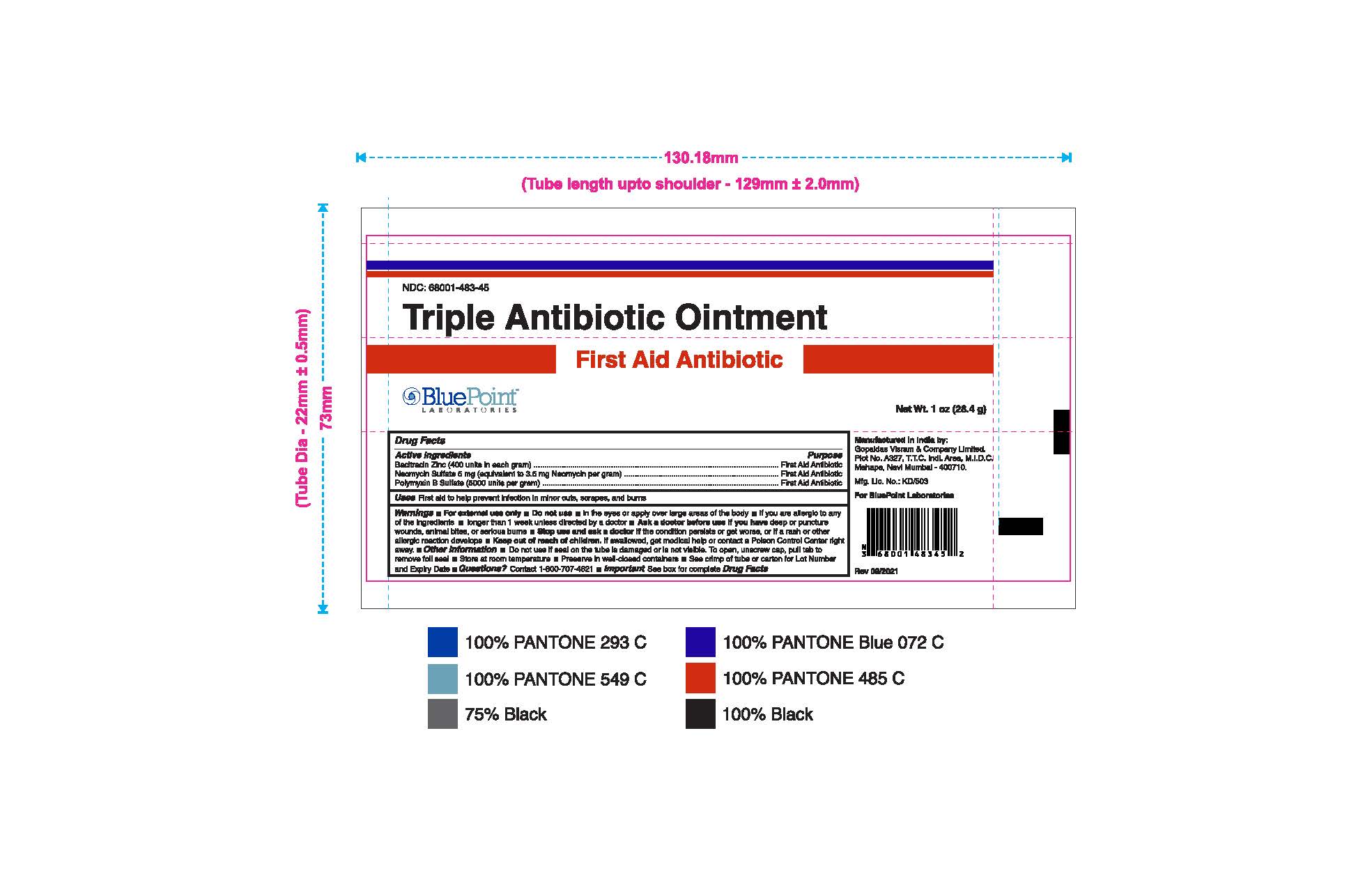 DRUG LABEL: Triple Antibiotic
NDC: 68001-483 | Form: OINTMENT
Manufacturer: BluePoint Laboratories
Category: otc | Type: HUMAN OTC DRUG LABEL
Date: 20240131

ACTIVE INGREDIENTS: NEOMYCIN SULFATE 3.5 mg/1 g; BACITRACIN ZINC 400 [iU]/1 g; POLYMYXIN B SULFATE 5000 [iU]/1 g
INACTIVE INGREDIENTS: WHITE PETROLATUM

Triple Antibiotic Ointment

Drug Facts

Active ingredients

Bacitracin Zinc (400 units in each gram)

Neomycin Sulfate 5mg (equivalent to 3.5mg Neomycin per gram)

Polymyxin B Sulfate (5000 units per gram)

Purpose

First Aid Antibiotics

Uses

First Aid to help prevent infection in minor cuts, scrapes and burns

Warnings

For external use only.

Do not use

- In the eyes or apply over large areas of the body
- If you are allergic to any of the ingredients
- Longer than 1 week unless directed by a doctor

Ask a doctor before use if you havedeep or puncture wounds, animal bites, or serious burns

Stop use and ask a doctor ifthe condition persists or gets worse, or if a rash or other allergic reaction develops

Keep out of reach of children. If swallowed, get medical help or contact a Poison Control Center right away.

Directions

Clean the affected area. Apply a small amount of this product (an amount equal to the surface area of the tip of a finger) on the area 1 to 3 times daily. May be covered with a sterile bandage.

Other information

- Do not use if seal on the tube is damaged or is not visible. To open, unscrew cap, pull tab to remove foil seal.
- Store at room temperatue
- Preserve in well-closed containers
- See crimp of tube or carton for Lot Number and Expiry Date

Inactive ingredients

White Petrolatum

Questions?

Contact 1-800-707-4621

Manufactured in India by:

Gopaldas Visram & Company Limited.

Plot No. A327, T.T.C. Indl. Area, M.L.D.C.

Mahape, Navi Mumbai - 400710.

Mfg. Lic. No.: KD/503

For BluePoint Laboratories

Rev 09/2021

Package Label - Principal Display Panel

Triple Antibiotic Ointment 0.5 oz NDC: 68001-483-46

PACKAGE LABEL

Triple Antibiotic Ointment 1 oz 68001-483-45